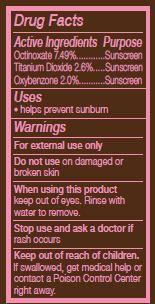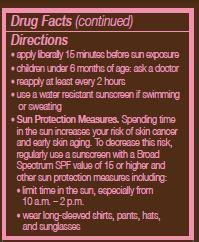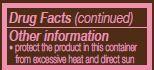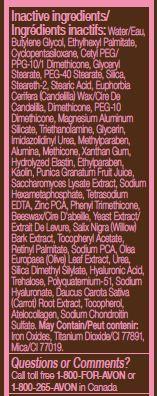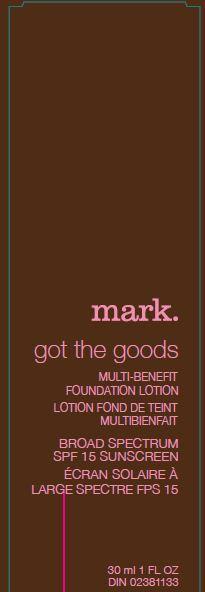 DRUG LABEL: mark got the goods
NDC: 10096-0281 | Form: LOTION
Manufacturer: New Avon LLC
Category: otc | Type: HUMAN OTC DRUG LABEL
Date: 20160217

ACTIVE INGREDIENTS: OCTINOXATE	 74.9 mg/1 mL; TITANIUM DIOXIDE	 26 mg/1 mL; OXYBENZONE 20 mg/1 mL

Active Ingredients
Octinoxate 7.49%.........
Titanium Dioxide 2.6%...
Oxybenzone 2.0%.........

Purpose
..... Sunscreen

..... Sunscreen

..... Sunscreen

Uses
■ helps prevent sunburn

WARNINGS
For external use only

Do not use on damaged or broken skin

When using this product keep out of eyes. Rinse with water to remove.

Stop use and ask a doctor if rash occurs

Keep out of reach of children. If swallowed, get medical help or contact a Poison Control Center right away.

Directions
• apply liberally 15 minutes before sun exposure
• children under 6 months of age: ask a doctor
• reapply at least every 2 hours
• use a water resistant sunscreen if swimming or sweating

• Sun Protection Measures. Spending time in the sun increases your risk of skin cancer and early skin aging. To decrease this risk, regularly use a sunscreen with a Broad Spectrum SPF value of 15 or higher and other sun protection measures including:
• limit time in the sun, especially from 10 a.m. – 2 p.m.
• wear long-sleeved shirts, pants, hats, and sunglasses

Other Information
■ protect the product in this container from excessive heat and direct sun.

INACTIVE INGREDIENT

Inactive ingredients: Water/Eau, Butylene Glycol, Ethylhexyl Palmitate, Cyclopentasiloxane, Cetyl PEG/PPG-10/1 Dimethicone, Glyceryl
Stearate, PEG-40 Stearate, Silica, Steareth-2, Stearic Acid, Euphorbia Cerifera (Candelilla) Wax/Cire De Candelilla, Dimethicone, PEG-10
Dimethicone, Magnesium Aluminum Silicate, Triethanolamine, Glycerin, Imidazolidinyl Urea, Methylparaben, Alumina, Methicone, Xanthan Gum, Hydrolyzed Elastin, Ethylparaben, Kaolin, Punica Granatum Fruit Juice, Saccharomyces Lysate Extract, Sodium Hexametaphosphate, Tetrasodium EDTA, Zinc PCA, Phenyl Trimethicone, Beeswax/Cire D'abeille, Yeast Extract/Extrait De Levure, Salix Nigra (Willow) Bark Extract, Tocopheryl Acetate, Retinyl Palmitate, Sodium PCA, Olea Europaea (Olive) Leaf Extract, Urea, Silica Dimethyl Silylate, Hyaluronic Acid, Trehalose, Polyquaternium-51, Sodium Hyaluronate, Daucus Carota Sativa (Carrot) Root Extract, Tocopherol, Atelocollagen, Sodium Chondroitin Sulfate. May Contain: Iron Oxides, Titanium Dioxide/CI 77891, Mica/CI 77019.

Questions or Comments? Call toll free 1-800-FOR-AVON or 1-800-265-AVON in Canada